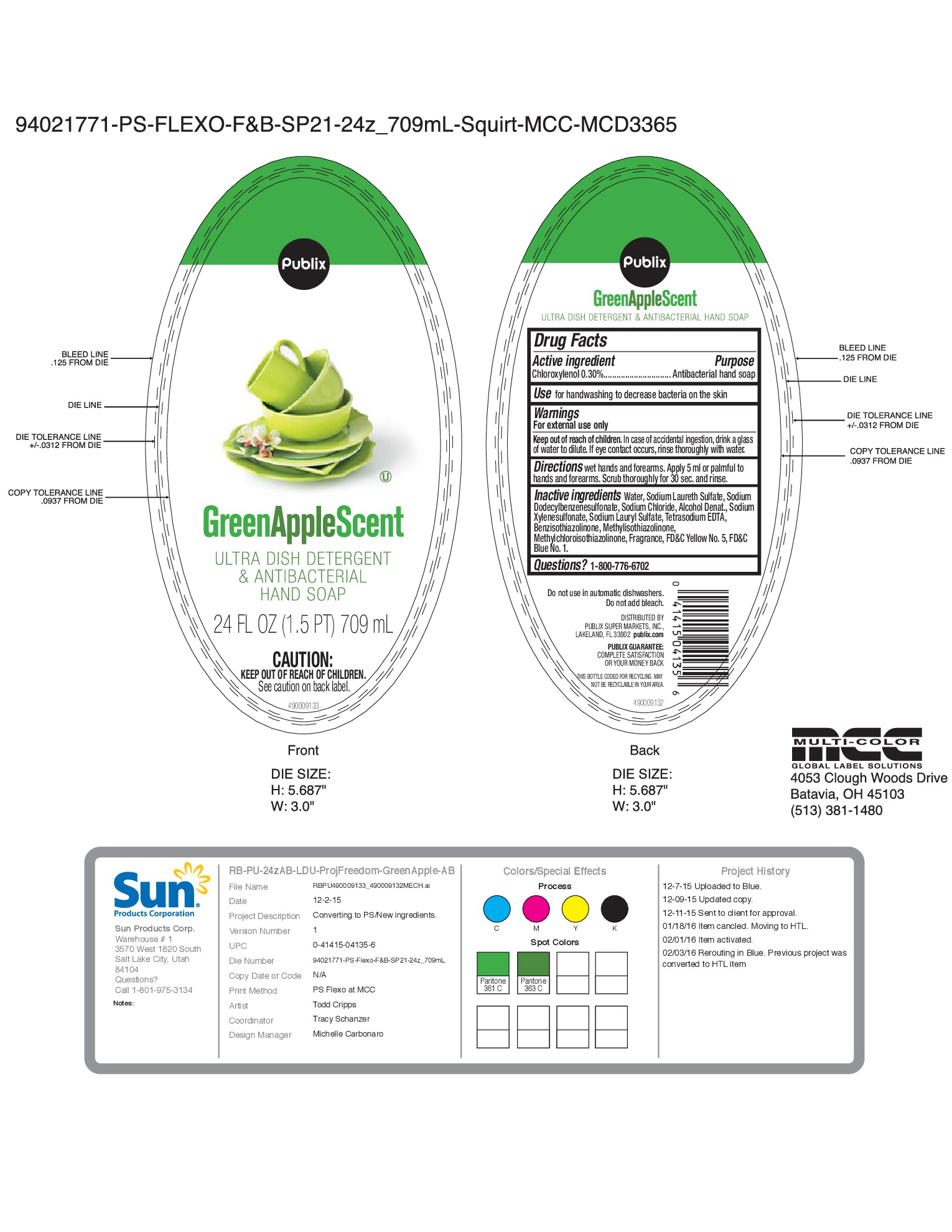 DRUG LABEL: Publix Green Apple Scent
NDC: 63691-031 | Form: SOAP
Manufacturer: Sun Products Corporation
Category: otc | Type: HUMAN OTC DRUG LABEL
Date: 20160630

ACTIVE INGREDIENTS: CHLOROXYLENOL 0.3 g/100 mL
INACTIVE INGREDIENTS: EDETATE SODIUM; FD&C YELLOW NO. 5; SODIUM DODECYLBENZENESULFONATE; SODIUM CHLORIDE; FD&C BLUE NO. 1; SODIUM XYLENESULFONATE; BENZISOTHIAZOLINONE; WATER; ALCOHOL; SODIUM LAURYL SULFATE; METHYLISOTHIAZOLINONE; METHYLCHLOROISOTHIAZOLINONE; SODIUM LAURETH SULFATE

Publix

Green Apple Scent

Ultra Dish Detergent & Antibacterial Hand Soap

Active Ingredient

Chloroxylenol 0.30%

Purpose

Antibacterial hand soap

Use

for handwashing to decrease bacteria on the skin

Warnings

For external use only

Keep out of reach of children.

In case of accidental ingestion, drink a glass of water to dilute. If eye contact occurs, rinse thoroughly with water.

Directions

wet hands and forearms. Apply 5 ml of palmful to hands and forearms. Scrub thoroughly for 30 sec. and rinse.

Inactive ingredients

Water, Sodium Laureth Sulfate, Sodium Dodecylbenzenesulfonate, Sodium Chloride, Alcohol Denat., Sodium Xylenesulfonate, Sodium Lauryl Sulfate, Tetrasodium EDTA, Benzisothiazolinone, Methylisothiazolinone, Methychloroisothiazolinone, Fragrance, FD&C Yellow No. 5, FD&C Blue No. 1

Questions?

1-800-776-6702